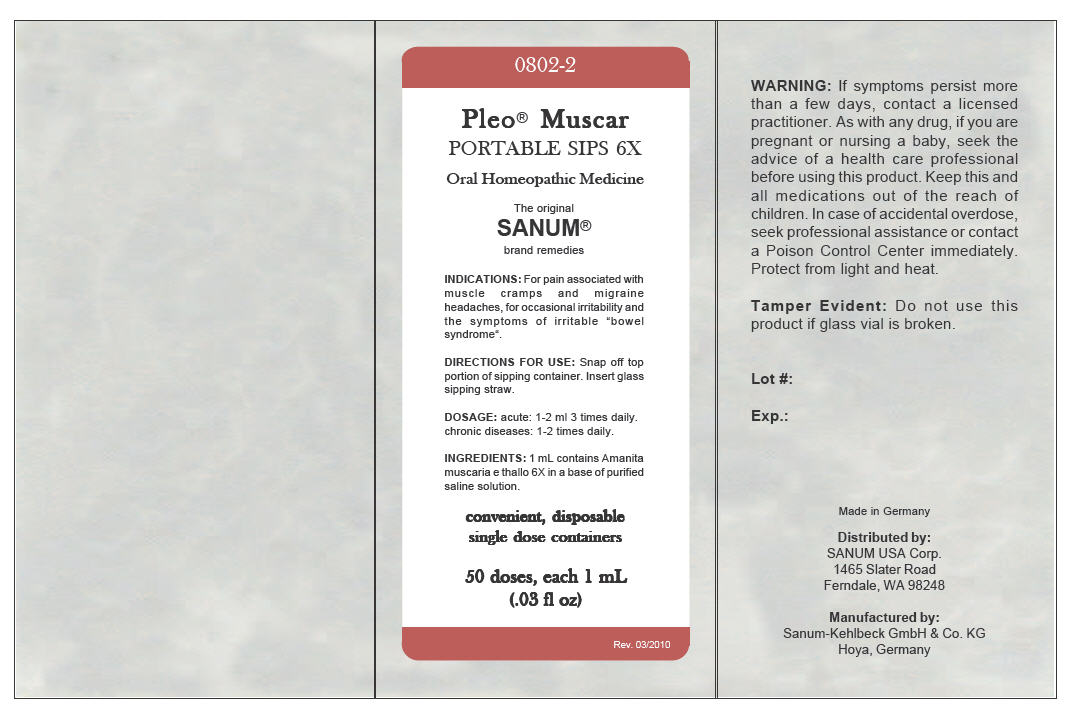 DRUG LABEL: Pleo Muscar
NDC: 60681-0802 | Form: LIQUID
Manufacturer: Sanum Kehlbeck GmbH & Co. KG
Category: homeopathic | Type: HUMAN OTC DRUG LABEL
Date: 20100603

ACTIVE INGREDIENTS: amanita muscaria var. muscaria 6 [hp_X]/1 mL
INACTIVE INGREDIENTS: sodium chloride; water

Pleo® Muscar
PORTABLE SIPS 6X

Oral Homeopathic Medicine

50 doses, each 1 mL
(.03 fl oz)

INDICATIONS

For pain associated with muscle cramps and migraine headaches, for occasional irritability and the symptoms of irritable "bowel syndrome".

DIRECTIONS FOR USE

Snap off top portion of sipping container. Insert glass sipping straw.

DOSAGE

acute: 1-2 ml 3 times daily. chronic diseases: 1-2 times daily.

INGREDIENTS

1 mL contains Amanita muscaria e thallo 6X in a base of purified saline solution.

WARNING

DO NOT USE

If symptoms persist more than a few days, contact a licensed practitioner. As with any drug, if you are pregnant or nursing a baby, seek the advice of a health care professional before using this product.

KEEP OUT OF REACH OF CHILDREN

Keep this and all medications out of the reach of children. In case of accidental overdose, seek professional assistance or contact a Poison Control Center immediately.

STORAGE AND HANDLING

Protect from light and heat.

Tamper Evident

Do not use this product if glass vial is broken.

Made in Germany

Distributed by:
SANUM USA Corp.
1465 Slater Road
Ferndale, WA 98248

Manufactured by:
Sanum-Kehlbeck GmbH & Co. KG
Hoya, Germany

Rev. 03/2010

PRINCIPAL DISPLAY PANEL - 1 mL Vial Carton

0802-2

Pleo® Muscar

PORTABLE SIPS 6X

Oral Homeopathic Medicine

The original
SANUM®
brand remedies

INDICATIONS: For pain associated with
muscle cramps and migraine
headaches, for occasional irritability and
the symptoms of irritable "bowel
syndrome".

DIRECTIONS FOR USE: Snap off top
portion of sipping container. Insert glass
sipping straw.

DOSAGE: acute: 1-2 ml 3 times daily.
chronic diseases: 1-2 times daily.

INGREDIENTS: 1 mL contains Amanita
muscaria e thallo 6X in a base of purified
saline solution.

convenient, disposable
single dose containers

50 doses, each 1 mL
(.03 fl oz)

Rev. 03/2010